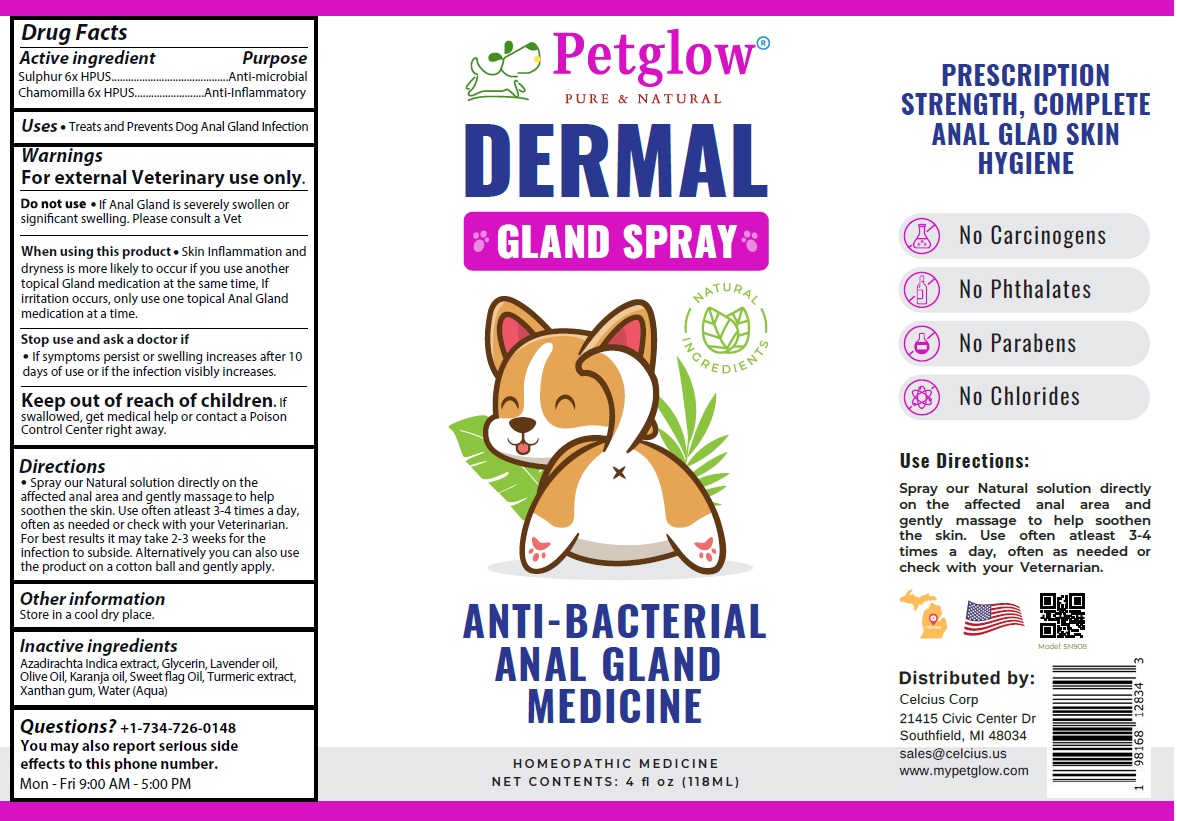 DRUG LABEL: Petglow DERMAL GLAND
NDC: 83819-009 | Form: SPRAY
Manufacturer: Celcius Corp.
Category: homeopathic | Type: OTC ANIMAL DRUG LABEL
Date: 20260216

ACTIVE INGREDIENTS: SULFUR 6 [hp_X]/118 mL; CHAMOMILE 6 [hp_X]/118 mL
INACTIVE INGREDIENTS: AZADIRACHTA INDICA SEED OIL; GLYCERIN; LAVENDER OIL; OLIVE OIL; KARUM SEED OIL; CALAMUS OIL; TURMERIC; XANTHAN GUM; WATER

Petglow® DERMAL GLAND SPRAY

Active ingredient

Sulphur 6x HPUS
Chamomilla 6x HPUS

Purpose

Anti-microbial
Anti-Inflammatory

Uses

• Treats and Prevents Dog Anal Gland Infection

Warnings

For external Veterinary use only.

Do not use • If Anal Gland is severely swollen or significant swelling. Please consult a Vet

When using this product • Skin Inflammation and dryness is more likely to occur if you use another topical Gland medication at the same time, If irritation occurs, only use one topical Anal Gland medication at a time.

Stop use and ask a doctor if
• If symptoms persist or swelling increases after 10 days of use or if the infection visibly increases.

Keep out of reach of children. If swallowed, get medical help or contact a Poison Control Center right away.

Directions

• Spray our Natural solution directly on the affected anal area and gently massage to help soothen the skin. Use often atleast 3-4 times a day, often as needed or check with your Veterinarian. For best results it may take 2-3 weeks for the infection to subside. Alternatively you can also use the product on a cotton ball and gently apply.

Other information

Store in a cool dry place.

Inactive ingredients

Azadirachta Indica extract, Glycerin, Lavender oil, Olive Oil, Karanja oil, Sweet flag Oil, Turmeric extract, Xanthan gum, Water (Aqua)

Questions?

+1-734-726-0148
You may also report serious side effects to this phone number.
Mon - Fri 9:00 AM - 5:00 PM

PURE & NATURAL

NATURAL INGREDIENTS

ANTI-BACTERIAL ANAL GLAND MEDICINE

HOMEOPATHIC MEDICINE

PRESCRIPTION STRENGTH, COMPLETE ANAL GLAD SKIN HYGIENE

No Carcinogens
No Phthalates
No Parabens
No Chlorides

Distributed by:
Celcius Corp
21415 Civic Center Dr
Southfield, MI 48034
sales@celcius.us
www.mypetglow.com